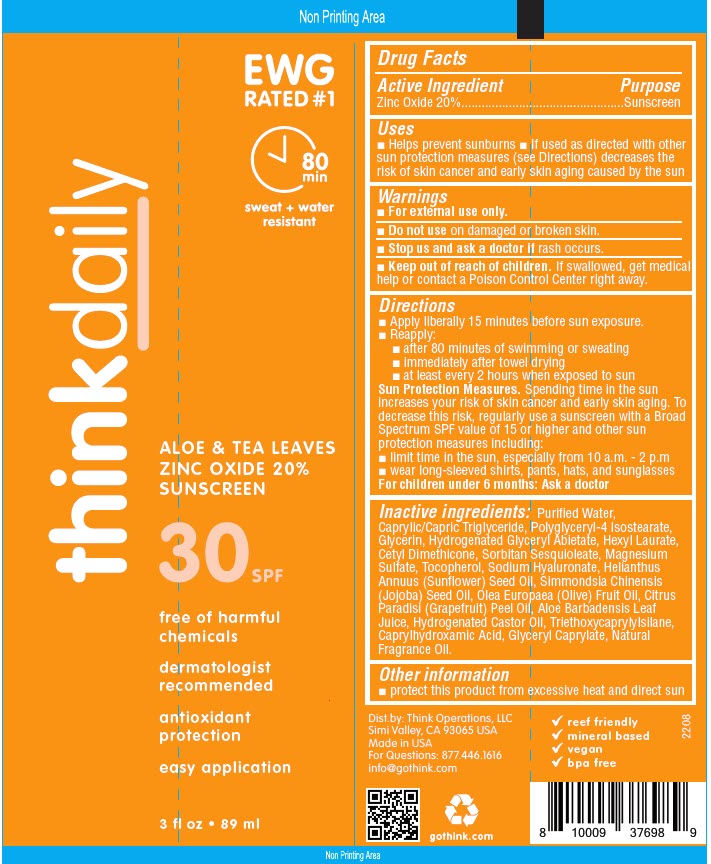 DRUG LABEL: Think Aloe and Tea Leaves 
NDC: 60781-4698 | Form: LOTION
Manufacturer: thinkOperations,LLC
Category: otc | Type: HUMAN OTC DRUG LABEL
Date: 20230202

ACTIVE INGREDIENTS: ZINC OXIDE 200 mg/1 mL
INACTIVE INGREDIENTS: WATER; MEDIUM-CHAIN TRIGLYCERIDES; POLYGLYCERYL-4 ISOSTEARATE; GLYCERIN; HYDROGENATED METHYL ABIETATE; CETYL DIMETHICONE 150; HEXYL LAURATE; DIMETHICONE; HYDROGENATED CASTOR OIL; MAGNESIUM SULFATE, UNSPECIFIED FORM; SORBITAN SESQUIOLEATE; CAPRYLHYDROXAMIC ACID; GLYCERYL MONOCAPRYLATE; SUNFLOWER OIL; JOJOBA OIL; OLIVE OIL; .ALPHA.-TOCOPHEROL; HYALURONATE SODIUM

Think Aloe and Tea Leaves
Zinc oxide

Drug Facts

Active Ingredient

Zinc Oxide 20%

Purpose

Sunscreen

Uses

- Helps prevent sunburns
- If used as directed with other sun protection measures (see Directions) decreases the risk of skin cancer and early skin aging caused by the sun

Warnings

- For external use only.

- Do not use on damaged or broken skin.

STOP USE

- Stop us and ask a doctor if rash occurs.

- Keep out of reach of children. If swallowed, get medical help or contact a Poison Control Center right away.

Directions

- Apply liberally 15 minutes before sun exposure.
- Reapply:
  - after 80 minutes of swimming or sweating
  - immediately after towel drying
  - at least every 2 hours when exposed to sun

Sun Protection Measures. Spending time in the sun increases your risk of skin cancer and early skin aging. To decrease this risk, regularly use a sunscreen with a Broad Spectrum SPF value of 15 or higher and other sun protection measures including:

- limit time in the sun, especially from 10 a.m. - 2 p.m
- wear long-sleeved shirts, pants, hats, and sunglasses

For children under 6 months: Ask a doctor

Inactive ingredients

Purified Water, Caprylic/Capric Triglyceride, Polyglyceryl-4 Isostearate, Glycerin, Hydrogenated Glyceryl Abietate, Hexyl Laurate, Cetyl Dimethicone, Sorbitan Sesquioleate, Magnesium Sulfate, Tocopherol, Sodium Hyaluronate, Helianthus Annuus (Sunflower) Seed Oil, Simmondsia Chinensis (Jojoba) Seed Oil, Olea Europaea (Olive) Fruit Oil, Citrus Paradisi (Grapefruit) Peel Oil, Aloe Barbadensis Leaf Juice, Hydrogenated Castor Oil, Triethoxycaprylylsilane, Caprylhydroxamic Acid, Glyceryl Caprylate, Natural Fragrance Oil.

Other information

- protect this product from excessive heat and direct sun

For Questions

877.446.1616

Dist.by: Think Operations, LLC
Simi Valley, CA 93065 USA

PRINCIPAL DISPLAY PANEL - 89 ml Tube Label

thinkdaily

EWG
RATED #1
80
min
sweat + water
resistant

ALOE & TEA LEAVES
ZINC OXIDE 20%
SUNSCREEN

30 SPF

free of harmful
chemicals

dermatologist
recommended

antioxidant
protection

easy application

3 fl oz • 89 ml